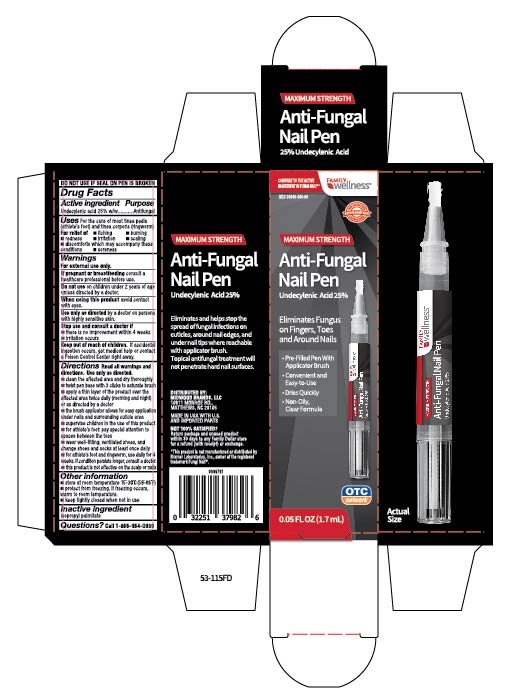 DRUG LABEL: Undecylenic Acid
NDC: 55319-055 | Form: LIQUID
Manufacturer: Family Dollar Services Inc.
Category: otc | Type: HUMAN OTC DRUG LABEL
Date: 20171215

ACTIVE INGREDIENTS: Undecylenic Acid 25 mg/1.7 mL
INACTIVE INGREDIENTS: ISOPROPYL PALMITATE

Antifungal Nail Pen

Active ingredient

Undecylenic acid 25%w/w

Purpose

Antifungal

Uses

For the cure of most tinea pedis (athlete's foot) and tinea corporis (ringworm)
For relief of:

itching
burning
redness
irritation
scaling
discomfort which may accompany these conditions
soreness

Warnings

For external use only.

If pregnant or breastfeeding

consult a healthcare professional before use.

Do not use

on children 2 years of age unless directed by a doctor.

When using this product

avoid contact with eyes.

Use only as directed

by a doctor on persons with highly sensitive skin.

Stop use and consult a doctor if

- there is no improvement within 4 weeks
- irritation occurs

Keep out of children.

If accidental ingestion occurs, get medical help or contact a Poison Control Center right away.

Directions

Read all warning and directions. Use only as directed.

clean the affected area and dry thoroughly
twist pen base with 3 clicks to saturate brush
apply a thin layer of the product over the affected area twice daily (morning and night) or as directed by the doctor
the brush applicator allows for easy application under nails and surrounding cuticle area
supervise children in the use of this product
for athlete's foot: pay special attention to spaces between the toes
wear well- fitting, ventilated shoes, and change shoes and socks at least once daily
for athlete's foot and ringworm, use daily for 4 weeks. If condition persists longer, consult a doctor.
this product is not effective on the scalp or nails

Other information

- store at room temperature 150 - 300C (590 - 860F)
- protect from freezing. if freezing occurs, warm to room temperature.
- keep tightly closed when not in use

Inactive ingredient

isopropyl palmitate

Questions?

Call 1-866-964-0939

Principal Display Panel

FAMILY WELLNESS

MAXIMUM STRENGTH

Anti- Fungal Nail Pen

Undecylenic Acid 25%

Eliminates Fungus on Fingers, Toes and Around Nails

- Pre- fikllled with applicator brush
- Covenient and Easy to use
- Dries Quickly
- Non - oily, clean Formula

0.05 FL. OZ (1.7 mL)